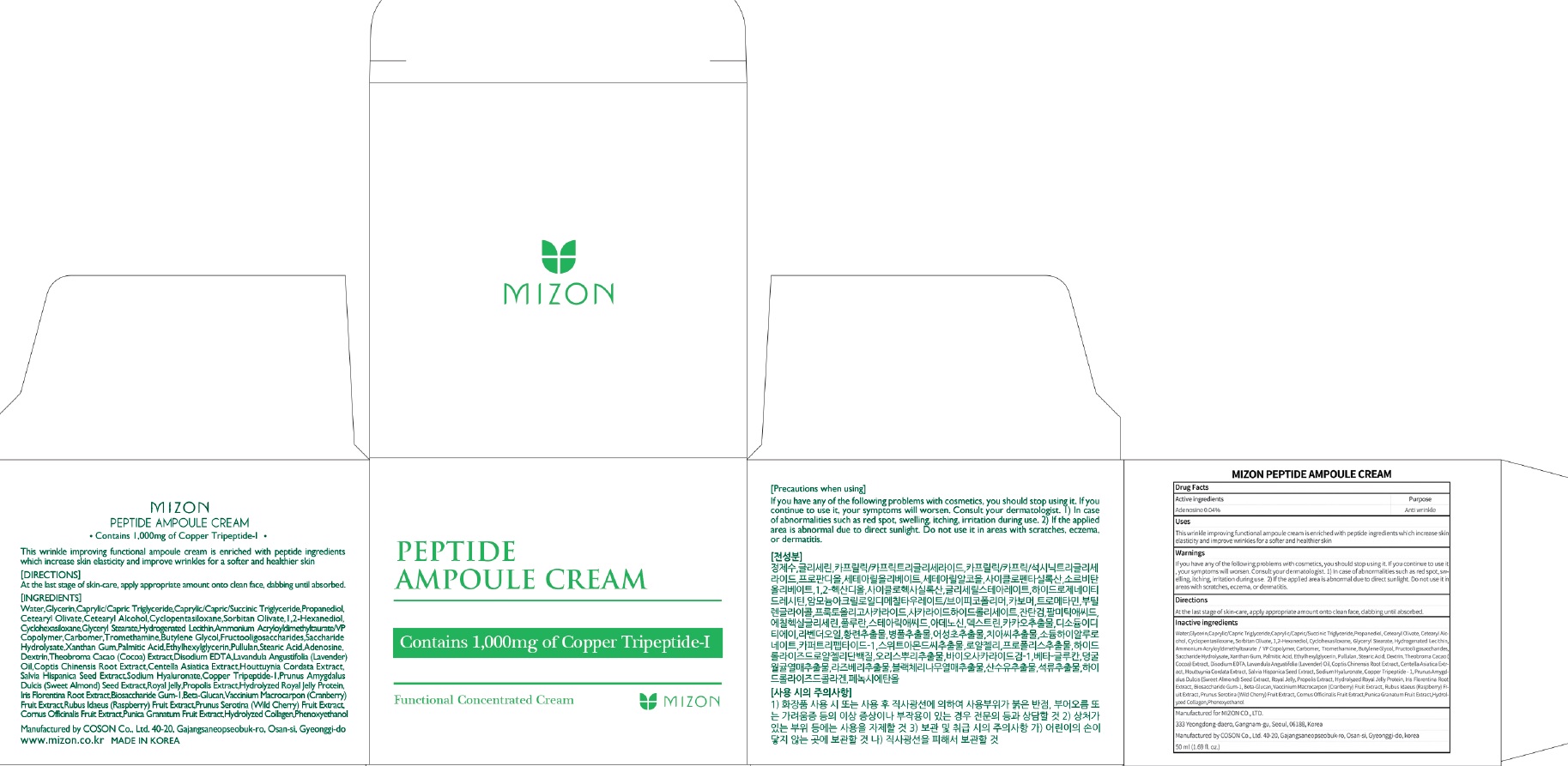 DRUG LABEL: MIZON PEPTIDE AMPOULE CREA M
NDC: 57718-320 | Form: CREAM
Manufacturer: MIZON CO.,LTD.
Category: otc | Type: HUMAN OTC DRUG LABEL
Date: 20180726

ACTIVE INGREDIENTS: Adenosine 0.02 g/50 mL
INACTIVE INGREDIENTS: Water; Glycerin

ACTIVE INGREDIENT

Active ingredients: Adenosine 0.04%

INACTIVE INGREDIENT

Inactive ingredients:

Water,Glycerin,Caprylic/Capric Triglyceride,Caprylic/Capric/Succinic Triglyceride,Propanediol, Cetearyl Olivate,Cetearyl Alcohol,Cyclopentasiloxane,Sorbitan Olivate,1,2-Hexanediol, Cyclohexasiloxane,Glyceryl Stearate,Hydrogenated Lecithin,Ammonium Acryloyldimethyltaurate/VP Copolymer,Carbomer,Tromethamine,Butylene Glycol,Fructooligosaccharides,Saccharide Hydrolysate,Xanthan Gum,Palmitic Acid,Ethylhexylglycerin,Pullulan,Stearic Acid, Dextrin,Theobroma Cacao (Cocoa) Extract,Disodium EDTA,Lavandula Angustifolia (Lavender) Oil,Coptis Chinensis Root Extract,Centella Asiatica Extract,Houttuynia Cordata Extract, Salvia Hispanica Seed Extract,Sodium Hyaluronate,Copper Tripeptide-1,Prunus Amygdalus Dulcis (Sweet Almond) Seed Extract,Royal Jelly,Propolis Extract,Hydrolyzed Royal Jelly Protein, Iris Florentina Root Extract,Biosaccharide Gum-1,Beta-Glucan,Vaccinium Macrocarpon (Cranberry) Fruit Extract,Rubus Idaeus (Raspberry) Fruit Extract,Prunus Serotina (Wild Cherry) Fruit Extract, Cornus Officinalis Fruit Extract,Punica Granatum Fruit Extract,Hydrolyzed Collagen,Phenoxyethanol

PURPOSE

Purpose: Anti wrinkle

WARNINGS

If you have any of the following problems with cosmetics, you should stop using it. If you continue to use it, your symptoms will worsen. Consult your dermatologist. 1) In case of abnormalities such as red spot, swelling, itching, irritation during use. 2) If the applied area is abnormal due to direct sunlight. Do not use it in areas with scratches, eczema, or dermatitis.

KEEP OUT OF REACH OF CHILDREN

Uses

This wrinkle improving functional ampoule cream is enriched with peptide ingredients which increase skin elasticity and improve wrinkles for a softer and healthier skin

Directions

At the last stage of skin-care, apply appropriate amount onto clean face, dabbing until absorbed.